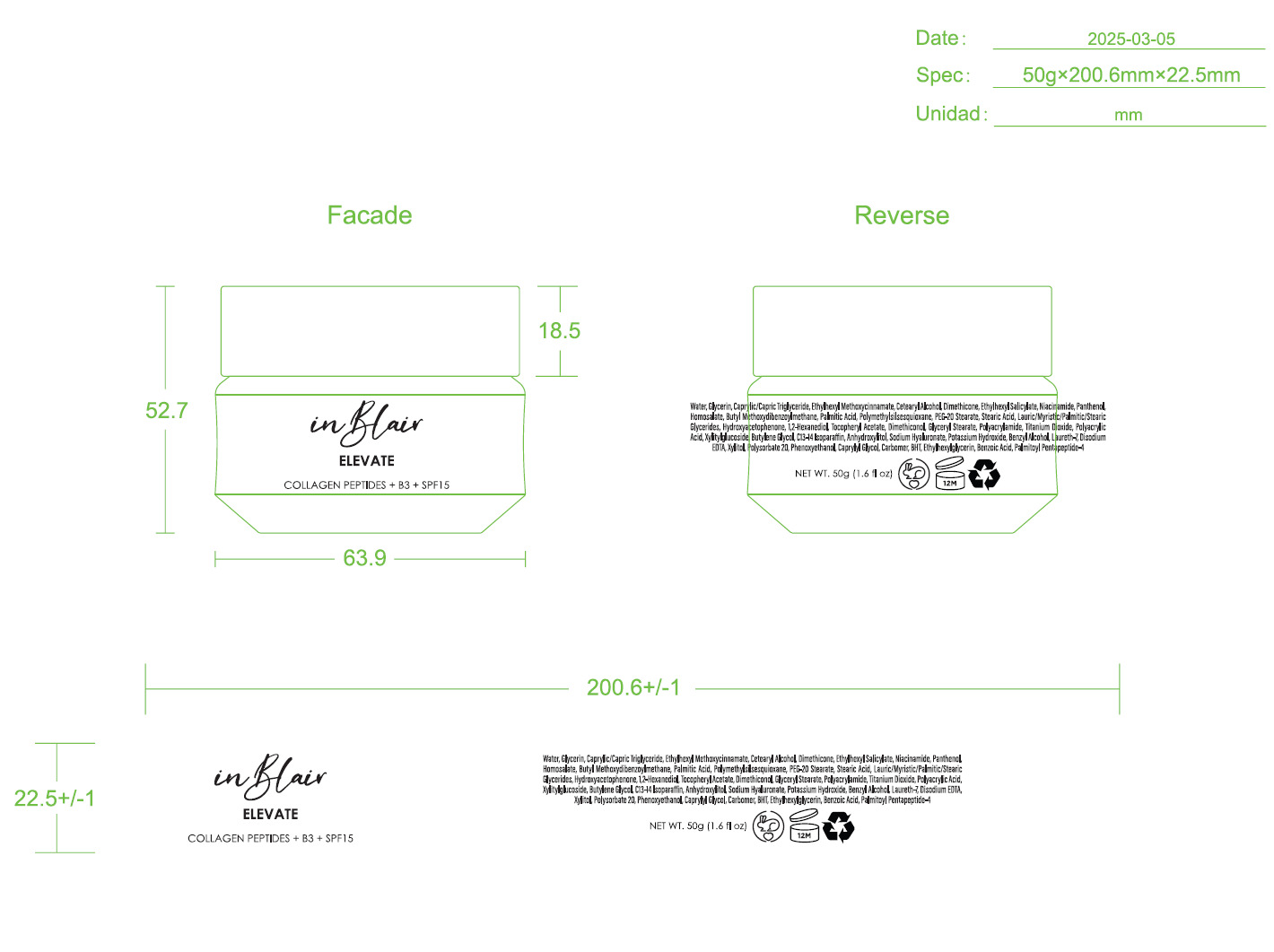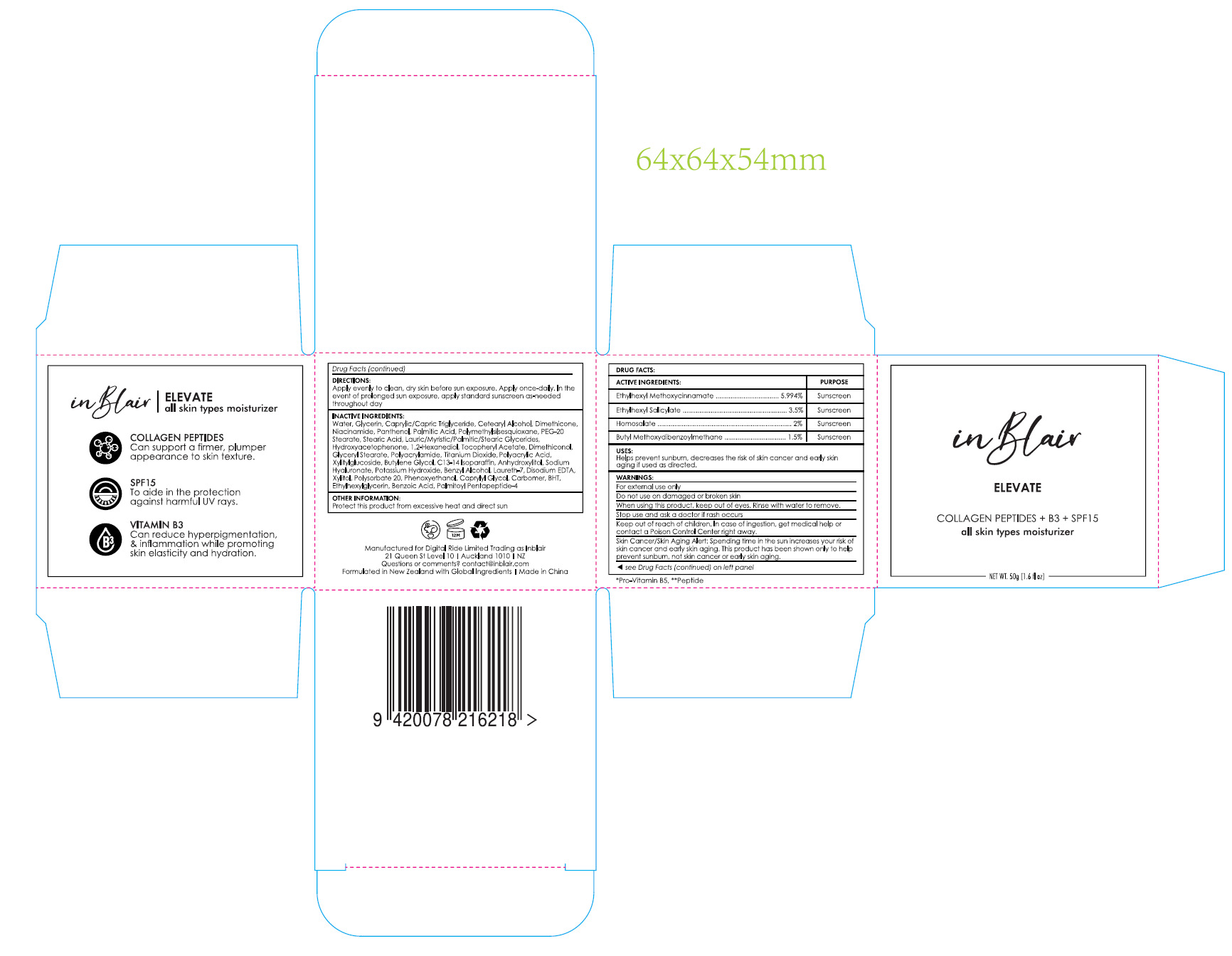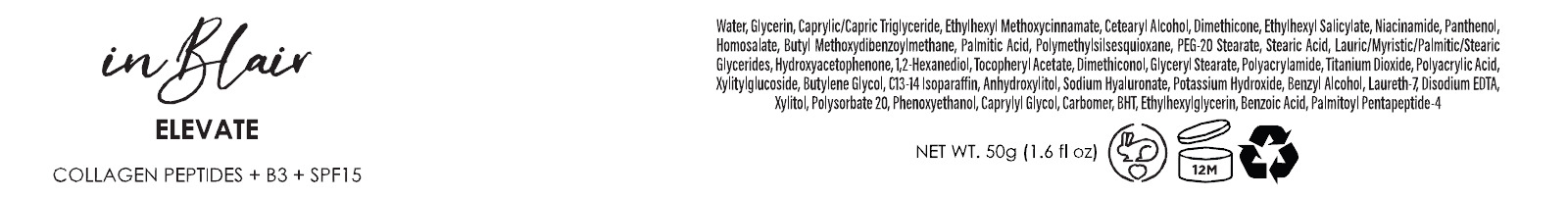 DRUG LABEL: Inblair Elevate SPF15 Moisturizer
NDC: 83447-014 | Form: CREAM
Manufacturer: Guangzhou Fantesy Biotechnology Co.,Ltd
Category: otc | Type: HUMAN OTC DRUG LABEL
Date: 20251207

ACTIVE INGREDIENTS: ETHYLHEXYL METHOXYCINNAMATE 5.994 g/100 g; BUTYL METHOXYDIBENZOYLMETHANE 1.5 g/100 g; HOMOSALATE 2 g/100 g; ETHYLHEXYL SALICYLATE 3.5 g/100 g
INACTIVE INGREDIENTS: CAPRYLYL GLYCOL; NIACINAMIDE; POLYACRYLAMIDE (1500 MW); TITANIUM DIOXIDE; C13-14 ISOPARAFFIN; PHENOXYETHANOL; PEG-20 STEARATE; HYDROXYACETOPHENONE; CARBOMER; 1,2-HEXANEDIOL; GLYCERYL STEARATE; POTASSIUM HYDROXIDE; POLYSORBATE 20; BHT; PANTHENOL; ETHYLHEXYLGLYCERIN; XYLITOL; LAURETH-7; WATER; GLYCERIN; CAPRYLIC/CAPRIC TRIGLYCERIDE; CETEARYL ALCOHOL; PALMITIC ACID; STEARIC ACID; LAURIC/MYRISTIC/PALMITIC/STEARIC GLYCERIDES; ALPHA-TOCOPHEROL ACETATE; BUTYLENE GLYCOL; SODIUM HYALURONATE; BENZYL ALCOHOL; DIMETHICONOL (2000 CST); BENZOIC ACID; POLYMETHYLSILSESQUIOXANE (4.5 MICRONS); ANHYDROXYLITOL; PALMITOYL PENTAPEPTIDE-4; POLYACRYLIC ACID (8000 MW); XYLITYLGLUCOSIDE; EDETATE DISODIUM; DIMETHICONE

83447-014

Active ingredients

Ethylhexyl Methoxycinnamate 5.994%
Ethylhexyl Salicylate 3.5%
Homosalate 2%
Butyl Methoxydibenzoylmethane 1.5%

Purpose

Sunscreen

Uses

Helps prevent sunburn, decreases the risk of skin cancer and early skin
aging if used as directed.

Warnings

For external use only

Do not use on damaged or broken skin

When using this product, keep out of eyes. Rinse with water to remove.

Stop use

Stop use and ask a doctor if rash occurs.

Keep out of reach of children. In case of ingestion, get medical help or
contact a Poison Control Center right away.

Directions

Apply evenly to clean, dry skin before sun exposure. Apply once-daily. In the
event of prolonged sun exposure, apply standard sunscreen as-needed
throughout day

Other information

Protect this product from excessive heat and direct sun

Inactive ingredients

Water, Glycerin, Caprylic/Capric Triglyceride, Cetearyl Alcohol, Dimethicone,
Niacinamide, Panthenol, Palmitic Acid, Polymethylsilsesquioxane,PEG-20
Stearate, Stearic Acid, Lauric/Myristic/Palmitic/Stearic Glycerides,
Hydroxyacetophenone,1,2-Hexanediol, Tocopheryl Acetate, Dimethiconol,
Glyceryl Stearate, Polyacrylamide, Titanium Dioxide, Polyacrylic Acid,
Xylitylglucoside, Butylene Glycol, C13-14 Isoparaffin, Anhydroxylitol, Sodium
Hyaluronate, Potassium Hydroxide, Benzyl Alcohol, Laureth-7, Disodium EDTA,
Xylitol, Polysorbate20, Phenoxyethanol, Caprylyl Glycol, Carbomer,BHT,
Ethylhexylglycerin, Benzoic Acid, Palmitoyl Pentapeptide-4